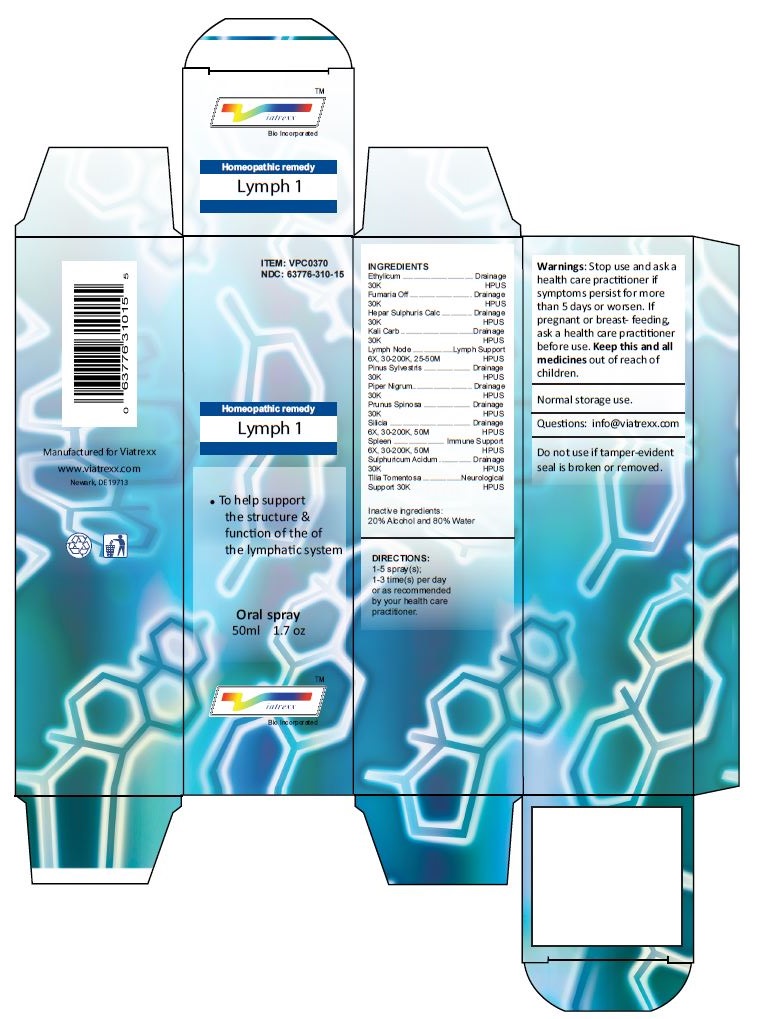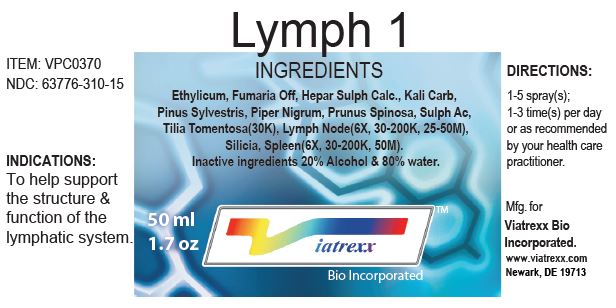 DRUG LABEL: Lymph 1
NDC: 63776-310 | Form: SPRAY
Manufacturer: VIATREXX BIO INCORPORATED
Category: homeopathic | Type: HUMAN OTC DRUG LABEL
Date: 20221130

ACTIVE INGREDIENTS: ALCOHOL 30 [kp_C]/1 mL; FUMARIA OFFICINALIS FLOWERING TOP 30 [kp_C]/1 mL; CALCIUM SULFIDE 30 [kp_C]/1 mL; POTASSIUM CARBONATE 30 [kp_C]/1 mL; BOS TAURUS LYMPH 200 [kp_C]/1 mL; PINUS SYLVESTRIS LEAFY TWIG 30 [kp_C]/1 mL; SUS SCROFA LYMPH 200 [kp_C]/1 mL; GREEN PEPPERCORN 30 [kp_C]/1 mL; PRUNUS SPINOSA FLOWER BUD 30 [kp_C]/1 mL; SILICON DIOXIDE 200 [kp_C]/1 mL; BOS TAURUS SPLEEN 200 [kp_C]/1 mL; SUS SCROFA SPLEEN 200 [kp_C]/1 mL; SULFURIC ACID 30 [kp_C]/1 mL; TILIA TOMENTOSA BUD 30 [kp_C]/1 mL
INACTIVE INGREDIENTS: WATER

Lymph 1

Active Ingredients

Ethylicum (30K), Fumaria Off (30K), Hepar Sulphuris Calc (30K), Kali Carb (30K), Lymph Node (6X, 30-200K, 25-50M), Pinus Sylvestris (30K), Piper Nigrum (30K), Prunus Spinosa (30K), Silicia (6X, 30-200K, 50M), Spleen (6X, 30-200K, 50M), Sulphuricum Acidum (30K), Tilia Tomentosa (30K)

Purpose:

Ethylicum | Drainage
Fumaria Off | Drainage
Hepar Sulphuris Calc | Drainage
Kali Carb | Drainage
Lymph Node | Lymph Support
Pinus Sylvestris | Drainage
Piper Nigrum | Drainage
Prunus Spinosa | Drainage
Silicia | Drainage
Spleen | Immune Support
Sulphuricum Acidum | Drainage
Tilia Tomentosa | Neurological

Uses

To help support the structure & function of the of the lymphatic system

Warnings

Stop use and ask a health care practitioner if symptoms persist for more than five days or worsen. If pregnant or breastfeeding, ask a health care practitioner before use.

Dosage

1-3 spray(s); 1-3 time(s) per day or as recommended by your health care practitioner.

KEEP OUT OF REACH OF CHILDREN

Keep this and all medicines out of reach of children.

Inactive ingredients

20% Alcohol and 80% Water.

Other Information

Normal storage use.
Do not use if tamper-evident seal is broken or removed.

Questions

info@viatrexx.com

Principal Display Panel

ITEM: VPC0370
NDC 63776-310-15
Homeopathic remedy
Lymph 1
• To help support the structure & function of the of the lymphatic system
Oral spray
50ml 1.7 oz
Viatrexx™ Bio Incorporated
Manufactured by Viatrexx
www.viatrexx.com
Newark, DE 19713

Lymph 1
50 ml
1.7 oz
Viatrexx™ Bio Incorporated
ITEM: VPC0370
NDC: 63776-310-15
INDICATIONS:
To help support the structure & function of the lymphatic system.
DIRECTIONS:
1-3 spray(s); 1-3 time(s) per day or as recommended by your health care practitioner.
Mfg. for
Viatrexx Bio Incorporated.
www.viatrexx.com
Newark, DE 19713